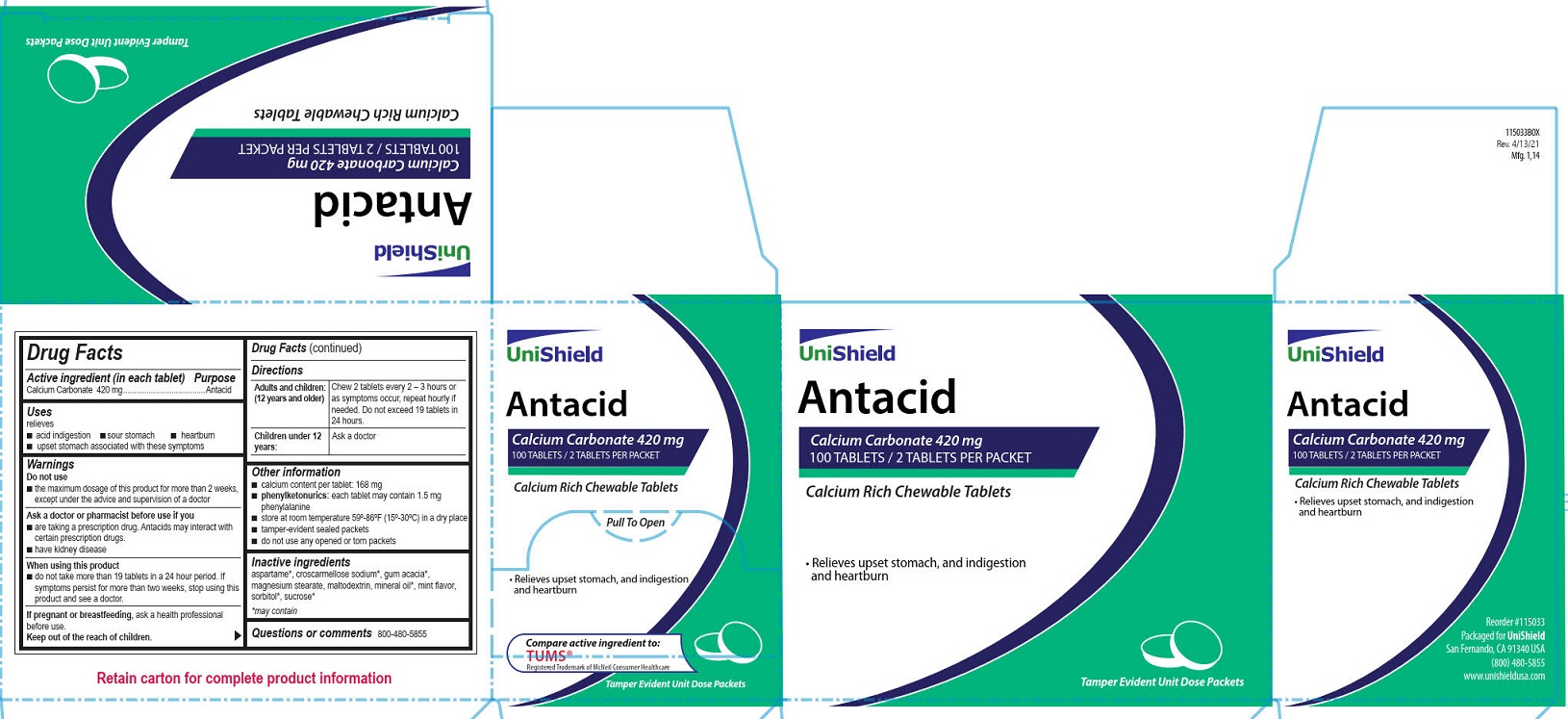 DRUG LABEL: Unishield Antacid
NDC: 49314-1023 | Form: TABLET, CHEWABLE
Manufacturer: Unishield
Category: otc | Type: HUMAN OTC DRUG LABEL
Date: 20250908

ACTIVE INGREDIENTS: CALCIUM CARBONATE 420 mg/1 1
INACTIVE INGREDIENTS: MAGNESIUM STEARATE; MALTODEXTRIN; SUCROSE; ACACIA

Unishield Antacid

Drug Facts

Active ingredient (in each tablet)

Calcium Carbonate 420 mg

Purpose

Antacid

Uses

relieves

■ acid indigestion

■ sour stomach

■ heartburn

■ upset stomach associated with these symptoms

Warnings

Do not use

■ the maximum dosage of this product for more than 2 weeks except under the advice and supervision of a doctor

Ask a doctor or pharmacist before use if

■ are taking a prescription drug. Antacids may interact with certain prescription drugs.

■ Have kidney disease

When using this product

■ do not take more than 19 tablets in a 24 hour period. If symptoms persist for more than 2 weeks, stop using this product and see a doctor.

PREGNANCY OR BREAST FEEDING

If pregnant or breast feeding, ask a health professional before use.

Keep out of the reach of children.

Directions

Adults and children: (12 years and older) Chew 2 tablets every 2 - 3 hours as symptoms occur, repeat hourly if needed. Do not exceed 19 tablets in 24 hours.

Children under 12 years: Ask a doctor

Other information

■calcium content per tablet: 168 mg

■ phenylketonurics: each tablet may contain 1.5 mg phenylalanine

■ store at room temperature 59º-86ºF (15º-30ºC) in a dry place

■ tamper-evident sealed packets

■ do not use any opened or torn packets

INACTIVE INGREDIENT

I nactive ingredients

aspartame*, croscarmellose sodium*, gum acacia*, magnesium stearate, maltodextrin, mineral oil*, mint flavor, sorbitol*, sucrose*

*may contain

Questions or comments? 1-800-480-5855

PACKAGE LABEL

Unishield

Antacid

Calcium Carbonate 420 mg

100 Tablets/2 Tablets Per Packet

Calcium Rich Chewable Tablets

Pull To Open

• Relieves upset stomach, and indigestion
and heartburn

Compare active ingredient to: TUMS®

Registered Trademark of McNeil Consumer Healthcare

Tamper Evident Unit Dose Packets